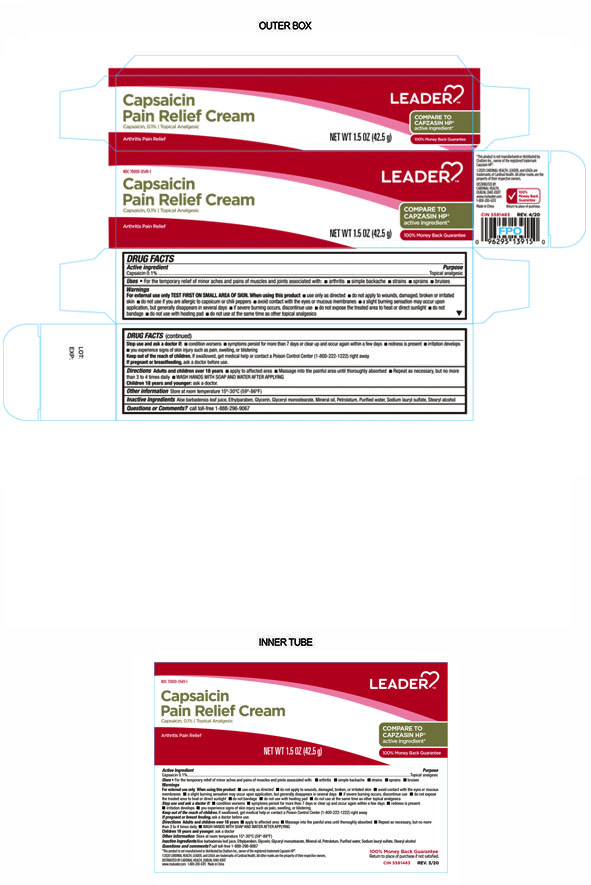 DRUG LABEL: Leader Capsaicin Pain Relief Cream
NDC: 70000-0549 | Form: CREAM
Manufacturer: Cardinal Health 110 dba LEADER
Category: otc | Type: HUMAN OTC DRUG LABEL
Date: 20251202

ACTIVE INGREDIENTS: CAPSAICIN 0.1 g/100 g
INACTIVE INGREDIENTS: GLYCERIN; GLYCERYL MONOSTEARATE; PETROLATUM; WATER; SODIUM LAURYL SULFATE; ALOE VERA LEAF; ETHYLPARABEN; MINERAL OIL; STEARYL ALCOHOL

Leader Capsaicin Pain Relief Cream

Active Ingredient

Capsaicin 0.1%

Purpose

Topical Analgesic

Warnings

For external use only: TEST FIRST ON SMALL AREA OF SKIN.

When using this product:

- Use only as directed
- Do not apply to wounds, damaged, broken or irritated sin
- Do not use if you are allergic to capsicum or chili peppers
- Avoid contact with the eyes or mucous membranes
- A slight burning sensation may occur upon application, but generally disappears in several days
- If severe burning occurs, discontinue use
- Do not expose the treated area to heat or direct sunlight
- Do not bandage
- Do not use with heating pad
- Do not use at the same time as other topical analgesics

Stop Use and Ask Doctor if:

- Condition worsens
- Symptoms persist for more than 7 days or clear up and occur again within a few days
- Redness is present
- irritation develops

Keep Out of the Reach of Children

If swallowed, get medical help or contact a Poison Control Center (1-800-222-1222) right away.

Uses

For the temporary relief of minor aches and pains of muscles and joints associated with:

- Arthritis
- Simple Backache
- Strains
- Sprains
- Bruises

If Pregnant or Breast Feeding

Ask a doctor before use

Directions

Adults and Children over 18 years:

- Apply to affected area
- Massage into the painful area until thoroughly absorbed
- Repeat as necessary but not more than 3 to 4 times daily
- WASH HANDS WITH SOAP AND WATER AFTER APPLYING

Children 18 years and younger:

Ask a doctor

Inactive Ingredients

Aloe barbadensis leaf juice, Ethylparaben, Glycerin, Clyceryl monostearate, Mineral Oil, Octadecyl alcohol, Petrolatum, Purified Water, Sodium lauryl Sulfate

Other Information

Store at room temperature 15°-30°F (59°-86°F)

Questions

1 (800) 200- 6313

Distributed by

Cardinal Health

Dublin, Ohio 43017

This product is not manufactured or distrubuted by Chattem Inc. owner of registered trademark Capzasin HP, 2020 Cardinal Health Leader and Logos are trademarks of Cardinal Health. All other marks are the property of their respective owners

www.myleader.com

Made in China